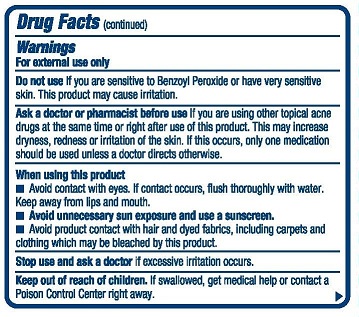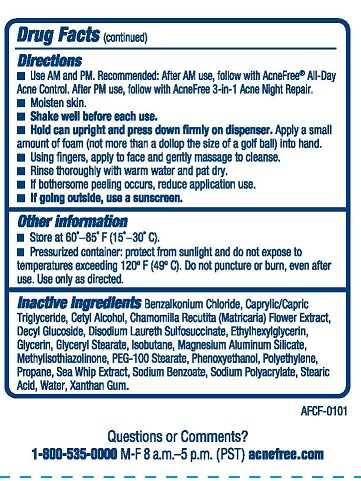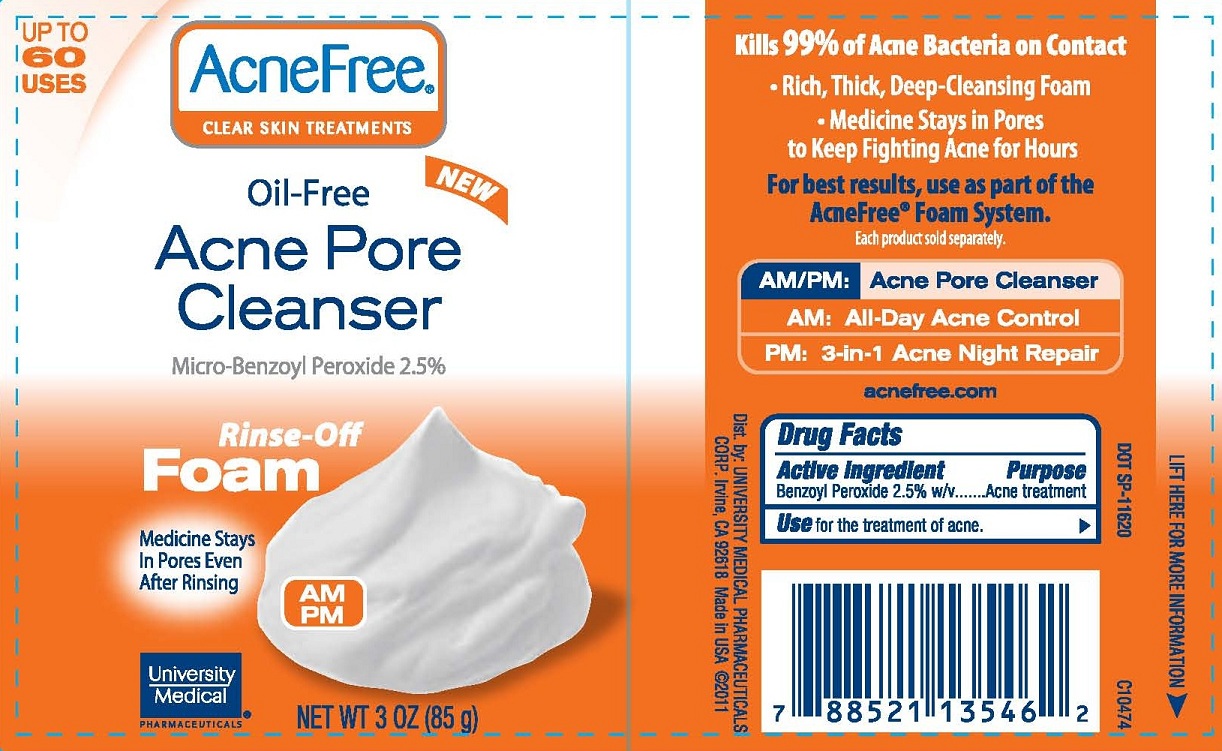 DRUG LABEL: AF Foam Clear Skin Acne Pore Cleanser
NDC: 50544-301 | Form: AEROSOL, FOAM
Manufacturer: University Medical Pharmaceuticals Corp
Category: otc | Type: HUMAN OTC DRUG LABEL
Date: 20111208

ACTIVE INGREDIENTS: Benzoyl Peroxide 2.5 g/100 g
INACTIVE INGREDIENTS: water; DISODIUM LAURETH SULFOSUCCINATE; GLYCERYL MONOSTEARATE; PEG-100 STEARATE; STEARIC ACID; glycerin; DECYL GLUCOSIDE; MATRICARIA RECUTITA; propane; BENZALKONIUM CHLORIDE; PSEUDOPTEROGORGIA ELISABETHAE; HIGH DENSITY POLYETHYLENE; MAGNESIUM ALUMINUM SILICATE; MEDIUM-CHAIN TRIGLYCERIDES; XANTHAN GUM; CETYL ALCOHOL; isobutane; SODIUM BENZOATE; PHENOXYETHANOL; ETHYLHEXYLGLYCERIN; METHYLISOTHIAZOLINONE

AF Foam CS Acne Pore Cleanser

Active Ingredient: Benzoyl Peroxide 2.5% w/v

Purpose: Acne Treatment

INDICATIONS AND USAGE

Use for the treatment of acne.

Warnings For external use only.

Do not use: If you are sensitive to Benzoyl Peroxide or have very sensitive skin. This product may cause irritation.

Ask a doctor or pharmacist before use: If you are using other topical acne drugs at the same time or right before use of this product. This may increase dryness, redness or irritation of the skin. If this occurs, only one medication should be used unless a doctor directs otherwise.

When using this product:

- Avoid contact with eyes. If contact occurs, flush thoroughly with water. Keep away from lips and mouth.
- Avoid unnecessary sun exposure and use a sunscreen.
- Avoid product with hair and dyed fabrics, including carpets and clothing which may be bleached by this product.

Stop use and ask a doctor: If excessive irritation occurs.

Keep out of reach of children: If swallowed, get medical help or contact a Poison Control Center right away.

Directions

- Use AM and PM. Recommended: After AM use, follow with AcneFree All-Day Acne Control. After PM use, follow with 3-in-1 Acne Night Repair.
- Moisten skin.
- Shake well before each use.
- Hold Can upright and press down firmly on dispenser. Apply a small amount of foam (not more than a dollop the size of a gold ball) into hand.
- Using fingers, apply to face and gently massage to cleanse.
- Rinse thoroughly with warn water and pat dry.
- If bothersome peeling occurs, reduce application use.
- If going outside, use a sunscreen.

INACTIVE INGREDIENT

Inactive ingredients: Benzylkonium Chloride, Caprylic/Capric Triglyceride, Cetyl Alcohol, Chamomilla Recutita (Matricaria) Flower Extract, Decyl Glucoside, Disodium Laureth Sulfosuccinate, Ethylhexylglycerin, Glycerin, Glyceryl Sterate, Isobutane, Magnesium Aluminum Silicate, Methylisothiazolinone, PEG-100 Stearate, Phenoxyethanol, Polyethylene, Propane, Sea Whip Extract, Sodium Benzoate, Sodium Polyacrylate, Stearic Acid, Water, Xanthan Gum.

Other Information

- Store at 60o-85oF (15o-30oC).
- Pressurized container: protect from sunlight and do not expose to temperatures exceeding 120oF(49oC). Do not puncture or birn, even after use. Use only as directed.

PACKAGE LABEL

AcneFree Clear Skin treatments
Oil-Free Acne Pore Cleanser
Micro-Benzoyl Peroxide 2.5%
Rinse-Off Foam
Medicine Stays in Pores Even After Rinsing